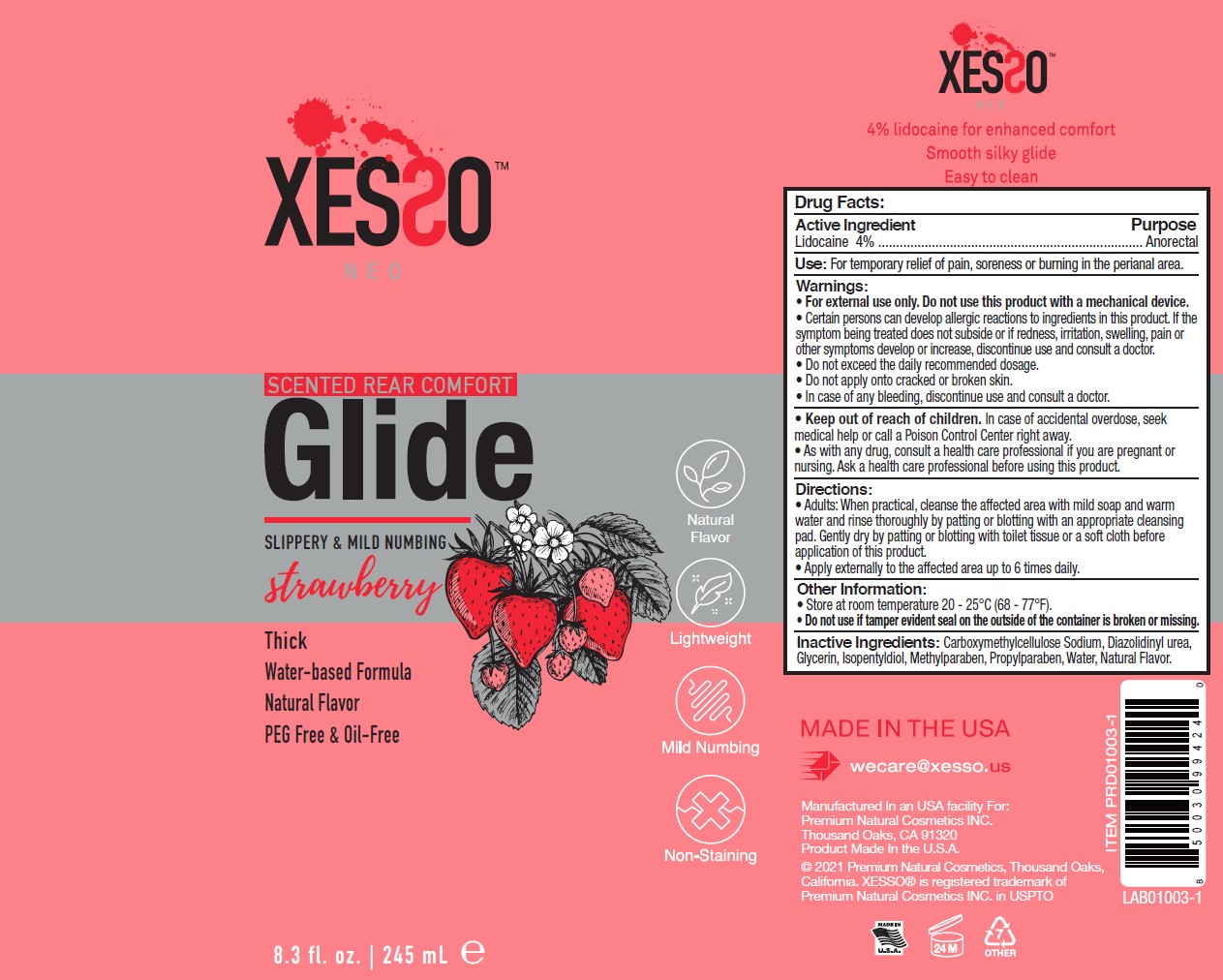 DRUG LABEL: Xesso Strawberry Rear Comfort Glide 4% Lidocaine
NDC: 81777-105 | Form: GEL
Manufacturer: Premium Natural Cosmetics Inc
Category: otc | Type: HUMAN OTC DRUG LABEL
Date: 20251017

ACTIVE INGREDIENTS: LIDOCAINE HYDROCHLORIDE 4.625 g/100 mL
INACTIVE INGREDIENTS: METHYLPARABEN; PROPYLPARABEN; GLYCERIN; DIAZOLIDINYL UREA; CARBOXYMETHYLCELLULOSE SODIUM, UNSPECIFIED FORM; ISOPENTYLDIOL; WATER

Xesso Strawberry Rear Comfort Glide 4% Lidocaine

Active Ingredient

Lidocaine 4%

Ask a doctor section

As with any drug, consult a health care professional if you are pregnant or nursing. Ask a health care professional before using this product.

Purpose

Anorectal

Use

For temporary relief of pain, soreness, or burning in the perianal area.

Keep out of reach of children. In case of accidental overdose, seek medical help or call a Poison Control Center right away.

Stop Use

Certain persons can develop allergic reactions to ingredients in this product. If the symptoms being treated does not subside or if redness, irritation, swelling, pain, or other symptoms develop or increase, discontinue use and consult a doctor.

Directions

- Adults: When practical, cleanse the affected area with mild soap and warm water and rinse thoroughly by patting or blotting with an appropriate cleansing pad. Gently dry by patting or blotting with toilet tissue or a soft cloth before application of this product.
- Apply externally to the affected area up to 6 times daily.

Warnings

• For external use only. Do not use this product with a mechanical device.
• Certain persons can develop allergic reactions to ingredients in this product. If the
symptom being treated does not subside or if redness, irritation, swelling, pain or
other symptoms develop or increase, discontinue use and consult a doctor.
• Do not exceed the daily recommended dosage.
• Do not apply onto cracked or broken skin.
• In case of any bleeding, discontinue use and consult a doctor.

Other information

• Store at room temperature 20 - 25°C (68 - 77°F).
• Do not use if tamper evident seal on the outside of the container is broken or missing.

Inactive Ingredients

Inactive Ingredients: Carboxymethylcellulose Sodium, Diazolidinyl urea, Glycerin, Isopentyldiol, Methylparaben, Propylparaben, Water, Natural Flavor.